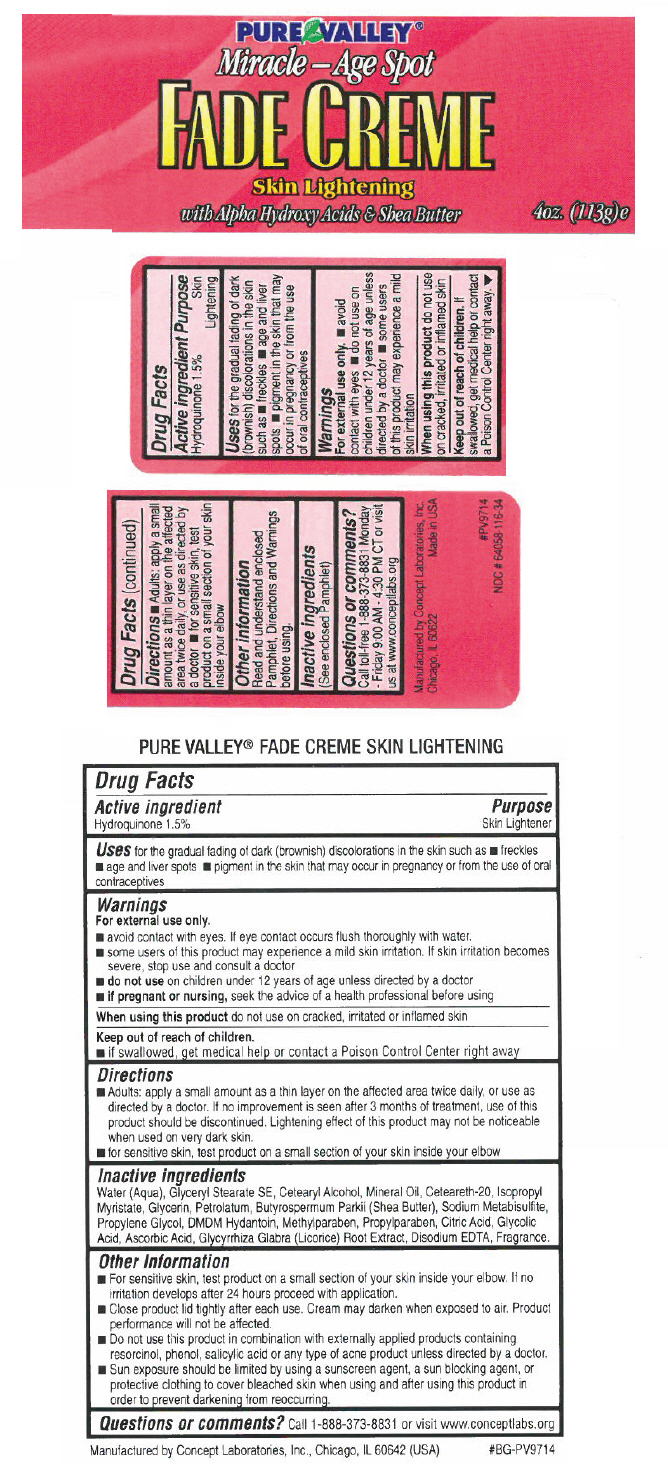 DRUG LABEL: Pure Valley Miracle Age Spot
NDC: 64058-116 | Form: LOTION
Manufacturer: Concept Laboratories, Inc.
Category: otc | Type: HUMAN OTC DRUG LABEL
Date: 20171027

ACTIVE INGREDIENTS: HYDROQUINONE 0.015 g/1 g
INACTIVE INGREDIENTS: GLYCERYL MONOSTEARATE; CETOSTEARYL ALCOHOL; POLYOXYL 20 CETOSTEARYL ETHER; PETROLATUM; MINERAL OIL; ISOPROPYL MYRISTATE; SHEA BUTTER; GLYCERIN; Water; ASCORBIC ACID; ANHYDROUS CITRIC ACID; GLYCOLIC ACID; DMDM HYDANTOIN; PROPYLENE GLYCOL; METHYLPARABEN; PROPYLPARABEN; EDETATE DISODIUM; GLYCYRRHIZA GLABRA; SODIUM METABISULFITE

Pure Valley® Miracle Age Spot

Drug Facts

Active ingredient

Hydroquinone 1.5%

Purpose

Skin Lightener

Uses

for the gradual fading of dark (brownish) discolorations in the skin such as

- freckles
- age and liver spots
- pigment in the skin that may occur in pregnancy or from the use of oral contraceptives

Warnings

For external use only.

- avoid contact with eyes. If eye contact occurs flush thoroughly with water.

STOP USE

- some users of this product may experience a mild skin irritation. If skin irritation becomes severe, stop use and consult a doctor

- do not use on children under 12 years of age unless directed by a doctor

PREGNANCY OR BREAST FEEDING

- if pregnant or nursing, seek the advice of a health professional before using

When using this product do not use on cracked, irritated or inflamed skin

Keep out of reach of children.

- if swallowed, get medical help or contact a Poison Control Center right away

Directions

- Adults: apply a small amount as a thin layer on the affected area twice daily, or use as directed by a doctor. If no improvement is seen after 3 months of treatment, use of this product should be discontinued. Lightening effect of this product may not be noticeable when used on very dark skin.
- for sensitive skin, test product on a small section of your skin inside your elbow

Inactive ingredients

Water (Aqua), Glyceryl Stearate SE, Cetearyl Alcohol, Mineral Oil, Ceteareth-20, Isopropyl Myristate, Glycerin, Petrolatum, Butyrospermum Parkii (Shea Butter), Sodium Metabisulfite, Propylene Glycol, DMDM Hydantoin, Methylparaben, Propylparaben, Citric Acid, Glycolic Acid, Ascorbic Acid, Glycyrrhiza Glabra (Licorice) Root Extract, Disodium EDTA, Fragrance.

Other Information

- For sensitive skin, test product on a small section of your skin inside your elbow. If no irritation develops after 24 hours proceed with application.
- Close product lid tightly after each use. Cream may darken when exposed to air. Product performance will not be affected.
- Do not use this product in combination with externally applied products containing resorcinol, phenol, salicylic acid or any type of acne product unless directed by a doctor.
- Sun exposure should be limited by using a sunscreen agent, a sun blocking agent, or protective clothing to cover bleached skin when using and after using this product in order to prevent darkening from reoccurring.

Questions or comments?

Call 1-888-373-8831 or visit www.conceptlabs.org

Manufactured by Concept Laboratories, Inc., Chicago, IL 60642 (USA)

PRINCIPAL DISPLAY PANEL - 113 g Jar Label

PURE VALLEY®

Miracle–Age Spot

FADE CREME

Skin Lightening

with Alpha Hydroxy Acids & Shea Butter

4oz. (113g)e